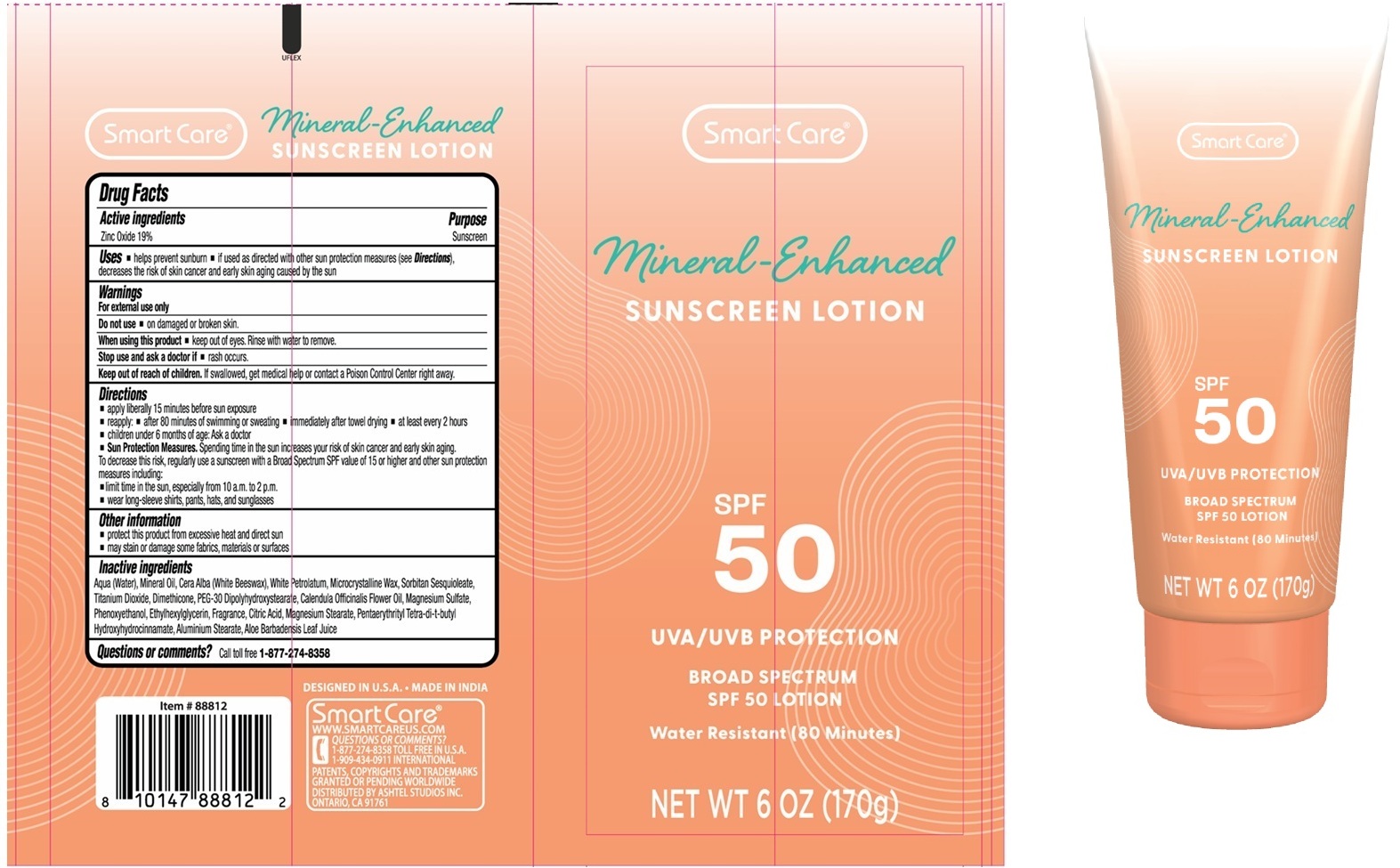 DRUG LABEL: Smart Care Mineral-Enhanced SUNSCREEN SPF 50
NDC: 70108-269 | Form: LOTION
Manufacturer: Ashtel Studios, Inc.
Category: otc | Type: HUMAN OTC DRUG LABEL
Date: 20260202

ACTIVE INGREDIENTS: ZINC OXIDE 19 g/100 g
INACTIVE INGREDIENTS: WATER; MINERAL OIL; WHITE WAX; WHITE PETROLATUM; MICROCRYSTALLINE WAX; SORBITAN SESQUIOLEATE; TITANIUM DIOXIDE; DIMETHICONE, UNSPECIFIED; PEG-30 DIPOLYHYDROXYSTEARATE (4000 MW); CALENDULA OFFICINALIS FLOWER; MAGNESIUM SULFATE, UNSPECIFIED FORM; PHENOXYETHANOL; ETHYLHEXYLGLYCERIN; CITRIC ACID MONOHYDRATE; MAGNESIUM STEARATE; PENTAERYTHRITOL TETRAKIS(3-(3,5-DI-TERT-BUTYL-4-HYDROXYPHENYL)PROPIONATE); ALUMINUM STEARATE; ALOE VERA LEAF JUICE

Smart Care® Mineral-Enhanced SUNSCREEN LOTION SPF 50

Active ingredients

Zinc Oxide 19%

Purpose

Sunscreen

Uses

• helps prevent sunburn • if used as directed with other sun protection measures (see Directions), decreases the risk of skin cancer and early skin aging caused by the sun

Warnings

For external use only

Do not use • on damaged or broken skin.

When using this product • keep out of eyes. Rinse with water to remove.

Stop use and ask a doctor if • rash occurs.

Keep out of reach of children. If swallowed, get medical help or contact a Poison Control Center right away.

Directions

• apply liberally 15 minutes before sun exposure
• reapply: • after 80 minutes of swimming or sweating • immediately after towel drying • at least every 2 hours
• children under 6 months of age: Ask a doctor
• Sun Protection Measures. Spending time in the sun increases your risk of skin cancer and early skin aging.
To decrease this risk, regularly use a sunscreen with a Broad Spectrum SPF value of 15 or higher and other sun protection measures including:
• limit time in the sun, especially from 10 a.m. to 2 p.m.
• wear long-sleeve shirts, pants, hats, and sunglasses

Other information

• protect this product from excessive heat and direct sun
• may stain or damage some fabrics, materials or surfaces

Inactive ingredients

Aqua (Water), Mineral Oil, Cera Alba (White Beeswax), White Petrolatum, Microcrystalline Wax, Sorbitan Sesquioleate, Titanium Dioxide, Dimethicone, PEG-30 Dipolyhydroxystearate, Calendula Officinalis Flower Oil, Magnesium Sulfate, Phenoxyethanol, Ethylhexylglycerin, Fragrance, Citric Acid, Magnesium Stearate, Pentaerythrityl Tetra-di-t-butyl Hydroxyhydrocinnamate, Aluminium Stearate, Aloe Barbadensis Leaf Juice

Questions or comments?

Call toll free 1-877-274-8358

UVA/UVB PROTECTION

BROAD SPECTRUM

Water Resistant (80 Minutes)

DESIGNED IN U.S.A. • MADE IN INDIA

Smart Care®
WWW.SMARTCAREUS.COM
1-909-434-0911 INTERNATIONAL
PATENTS, COPYRIGHTS AND TRADEMARKS GRANTED OR PENDING WORLDWIDE

DISTRIBUTED BY ASHTEL STUDIOS INC.
ONTARIO, CA 91761